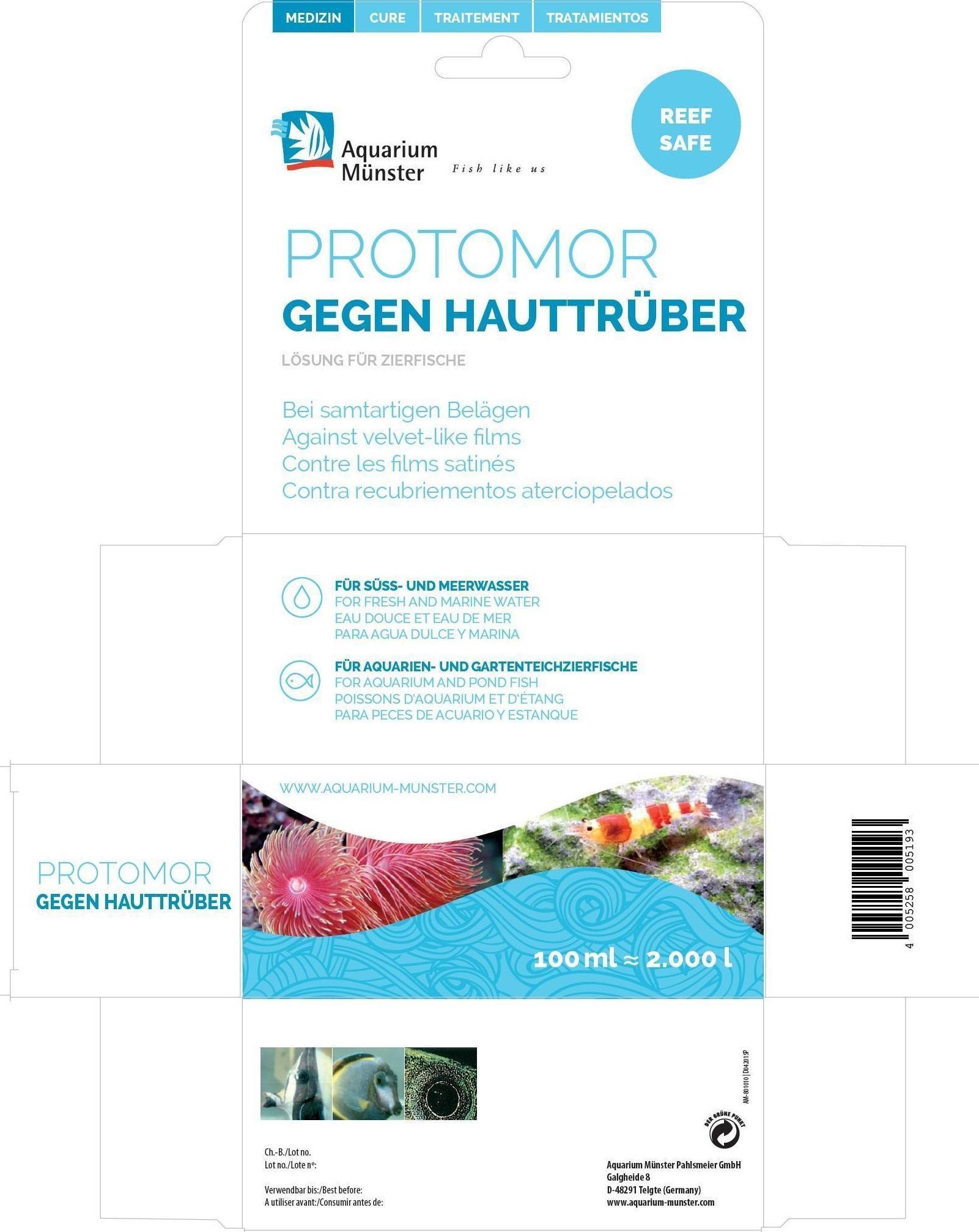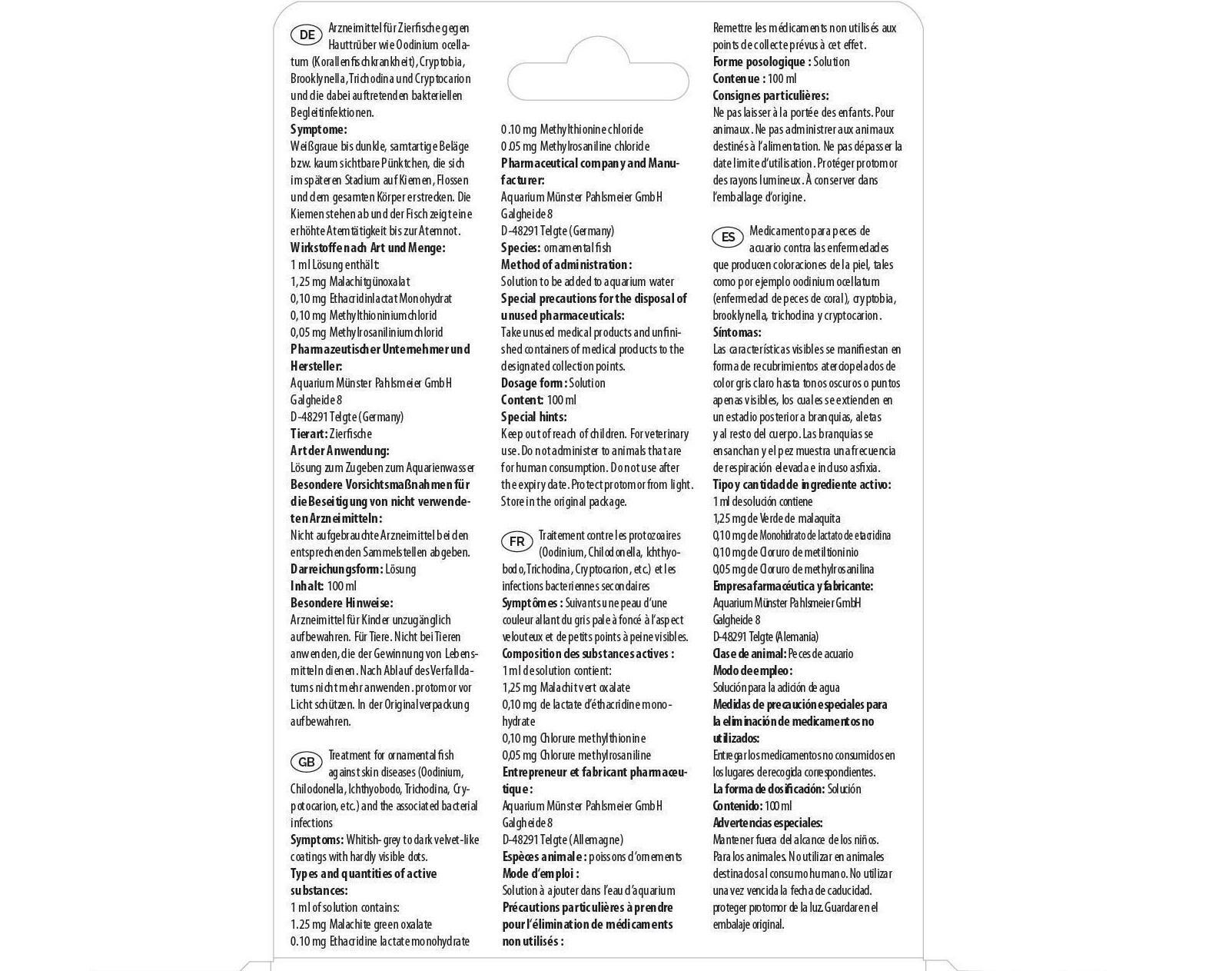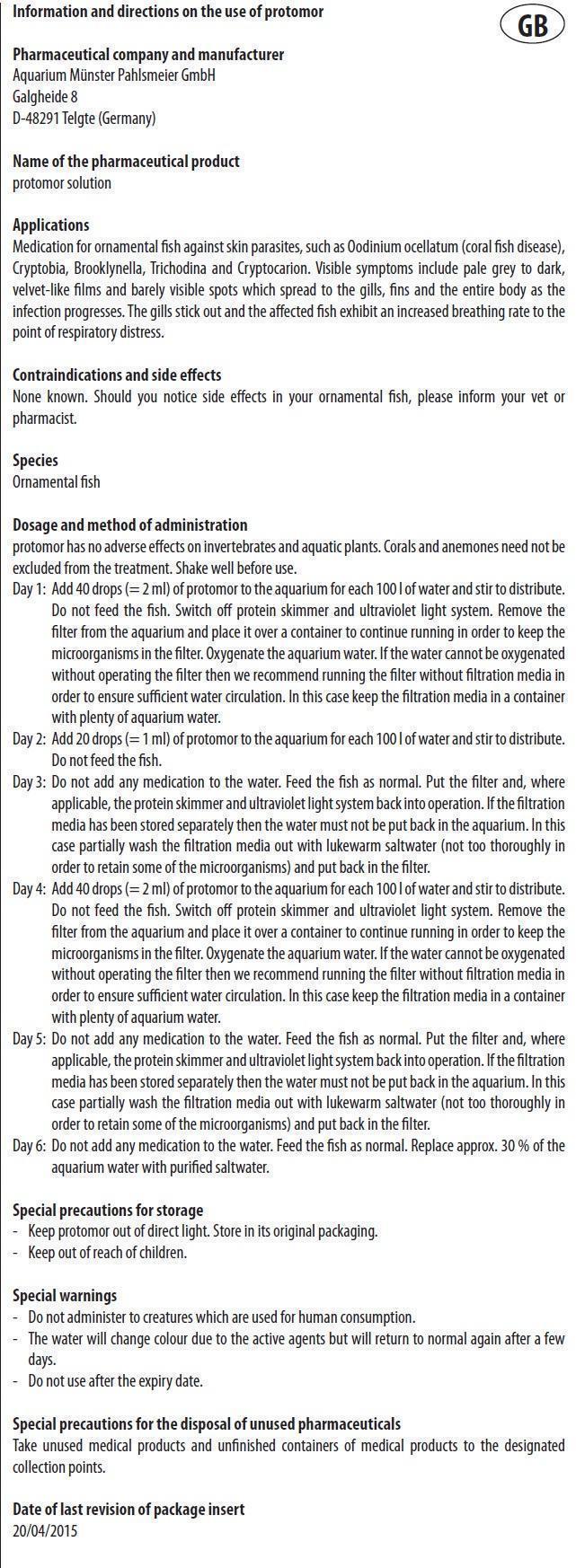 DRUG LABEL: Protomor
NDC: 86052-010 | Form: SOLUTION
Manufacturer: Aquarium Muenster Pahlsmeier GmbH
Category: animal | Type: OTC ANIMAL DRUG LABEL
Date: 20240419

ACTIVE INGREDIENTS: MALACHITE GREEN OXALATE 1.25 mg/1 mL; ETHACRIDINE LACTATE 0.10 mg/1 mL; METHYLENE BLUE ANHYDROUS 0.10 mg/1 mL; GENTIAN VIOLET 0.05 mg/1 mL

Protomor

Information and directions on the use of protomor

Pharmaceutical company and manufacturer
Aquarium Münster Pahlsmeier GmbH
Galgheide 8
D-48291 Telgte (Germany)

Name of the pharmaceutical product
protomor solution

Applications

Medication for ornamental fish against skin parasites, such as Oodinium ocellatum (coral fish disease), Cryptobia, Brooklynella, Trichodina and Cryptocarion. Visible symptoms include pale grey to dark, velvet-like films and barely visible spots which spread to the gills, fins and the entire body as the infection progresses. The gills stick out and the affected fish exhibit an increased breathing rate to the point of respiratory distress.

Types and quantities of active substances:

1 ml of solution contains:
1.25 mg Malachite green oxalate
0.10 mg Ethacridine lactate monohydrate
0.10 mg Methylthionine chloride
0.05 mg Methylrosaniline chloride

Contraindications and side effects

None known. Should you notice side effects in your ornamental fish, please inform your vet or pharmacist.

Species

Ornamental fish

Dosage and method of administration

protomor has no adverse effects on invertebrates and aquatic plants. Corals and anemones need not be excluded from the treatment. Shake well before use.
Day 1: Add 40 drops (= 2 ml) of protomor to the aquarium for each 100 l of water and stir to distribute. Do not feed the fish. Switch off protein skimmer and ultraviolet light system. Remove the filter from the aquarium and place it over a container to continue running in order to keep the microorganisms in the filter. Oxygenate the aquarium water. If the water cannot be oxygenated without operating the filter then we recommend running the filter without filtration media in order to ensure sufficient water circulation. In this case keep the filtration media in a container with plenty of aquarium water.
Day 2: Add 20 drops (= 1 ml) of protomor to the aquarium for each 100 l of water and stir to distribute. Do not feed the fish.
Day 3: Do not add any medication to the water. Feed the fish as normal. Put the filter and, where applicable, the protein skimmer and ultraviolet light system back into operation. If the filtration media has been stored separately then the water must not be put back in the aquarium. In this case partially wash the filtration media out with lukewarm saltwater (not too thoroughly in order to retain some of the microorganisms) and put back in the filter.
Day 4: Add 40 drops (= 2 ml) of protomor to the aquarium for each 100 l of water and stir to distribute. Do not feed the fish. Switch off protein skimmer and ultraviolet light system. Remove the filter from the aquarium and place it over a container to continue running in order to keep the microorganisms in the filter. Oxygenate the aquarium water. If the water cannot be oxygenated without operating the filter then we recommend running the filter without filtration media in order to ensure sufficient water circulation. In this case keep the filtration media in a container with plenty of aquarium water.
Day 5: Do not add any medication to the water. Feed the fish as normal. Put the filter and, where applicable, the protein skimmer and ultraviolet light system back into operation. If the filtration media has been stored separately then the water must not be put back in the aquarium. In this case partially wash the filtration media out with lukewarm saltwater (not too thoroughly in order to retain some of the microorganisms) and put back in the filter.
Day 6: Do not add any medication to the water. Feed the fish as normal. Replace approx. 30 % of the aquarium water with purified saltwater.

Special precautions for storage

- Keep protomor out of direct light. Store in its original packaging.

- Keep out of reach of children.

Special warnings

- Do not administer to creatures which are used for human consumption.
- The water will change colour due to the active agents but will return to normal again after a few days.
- Do not use after the expiry date.

Special precautions for the disposal of unused pharmaceuticals

Take unused medical products and unfinished containers of medical products to the designated collection points.